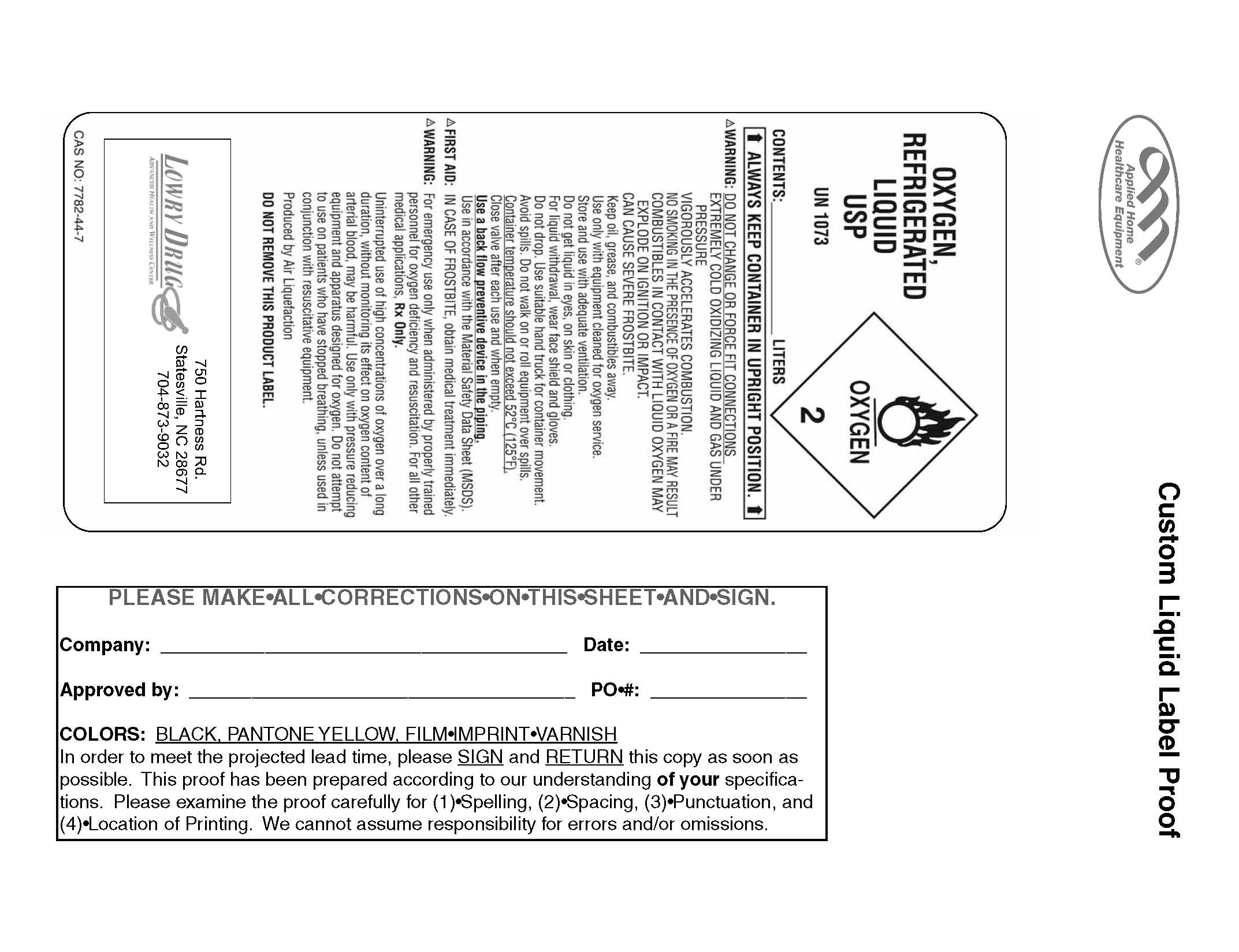 DRUG LABEL: Oxygen
NDC: 54582-0001 | Form: GAS
Manufacturer: Lowry Drug Company Inc. 
Category: prescription | Type: HUMAN PRESCRIPTION DRUG LABEL
Date: 20100105

ACTIVE INGREDIENTS: Oxygen 99 L/100 L

Oxygen